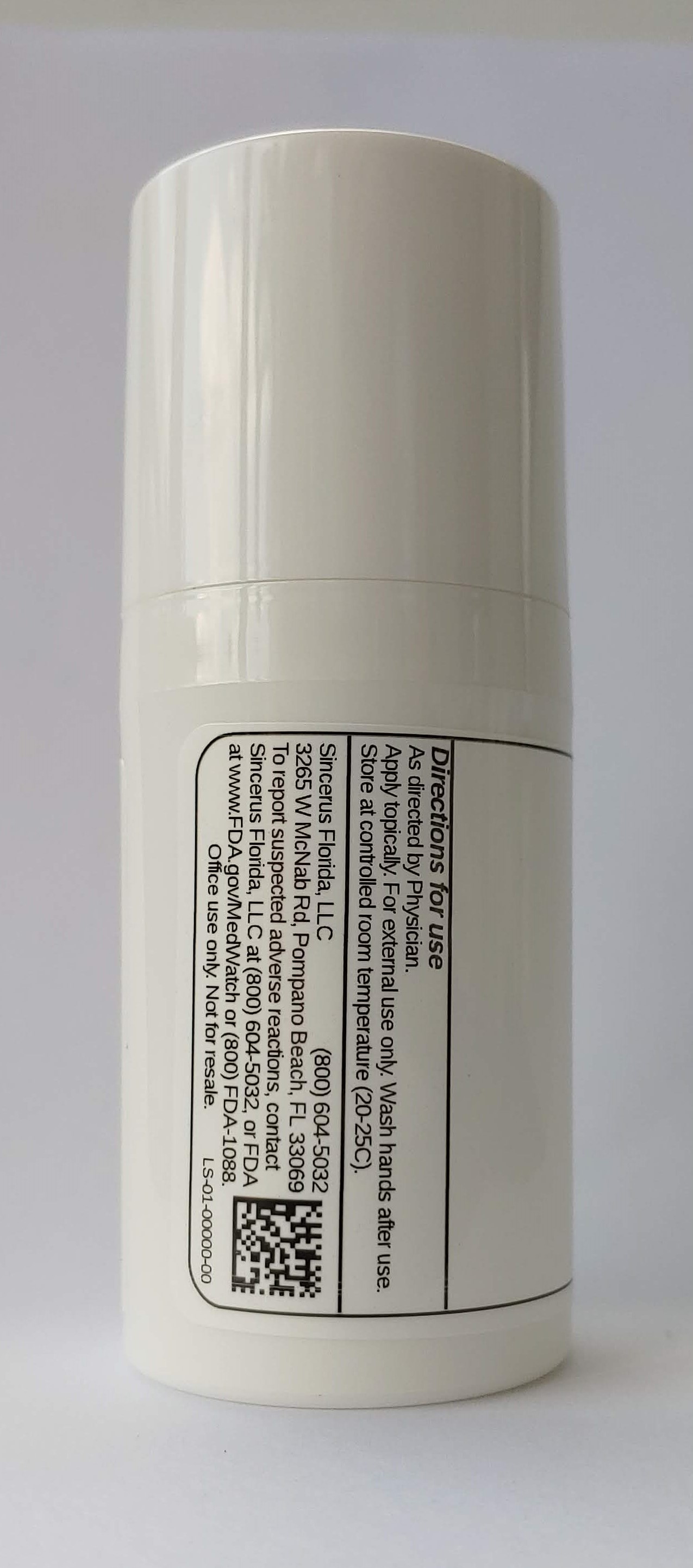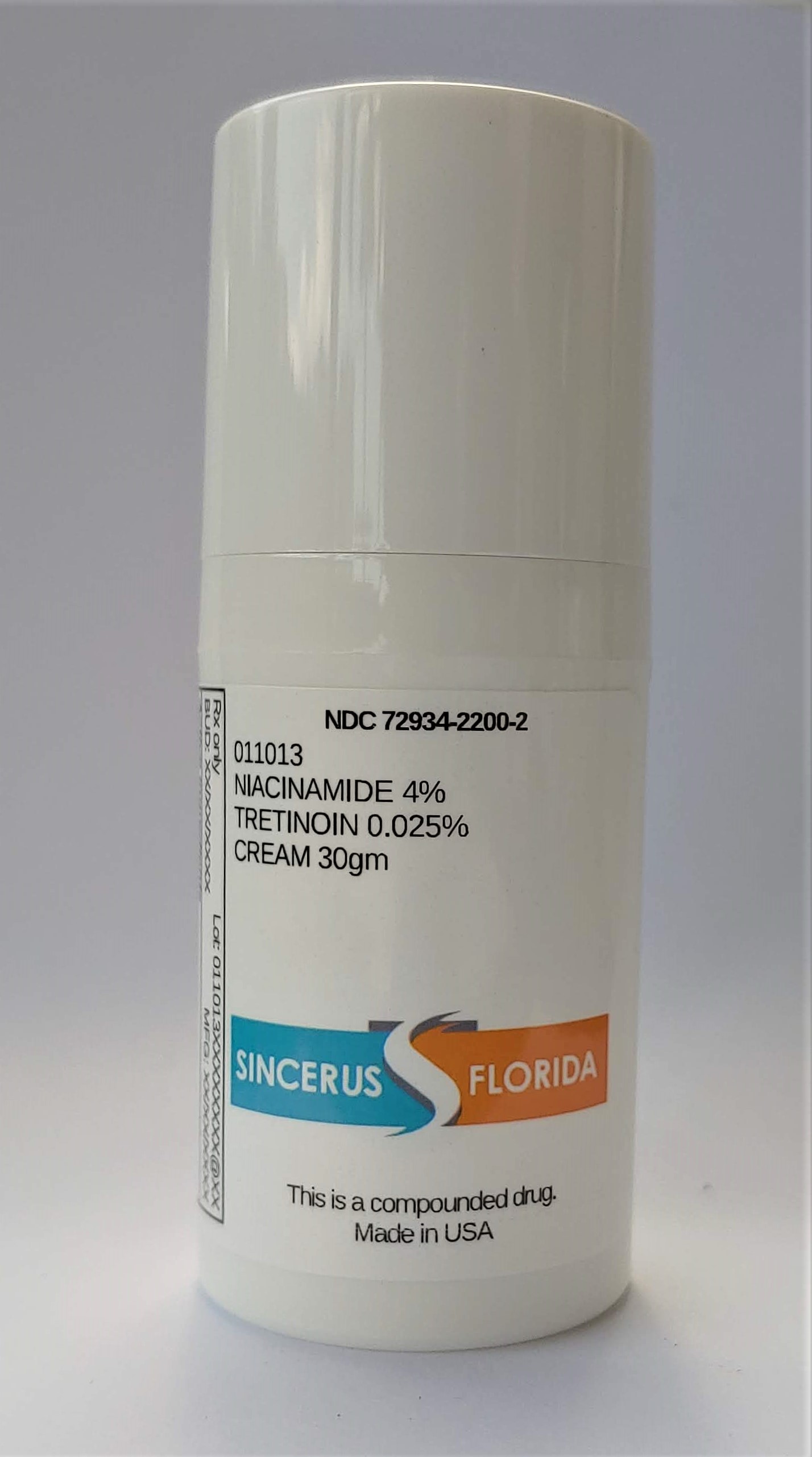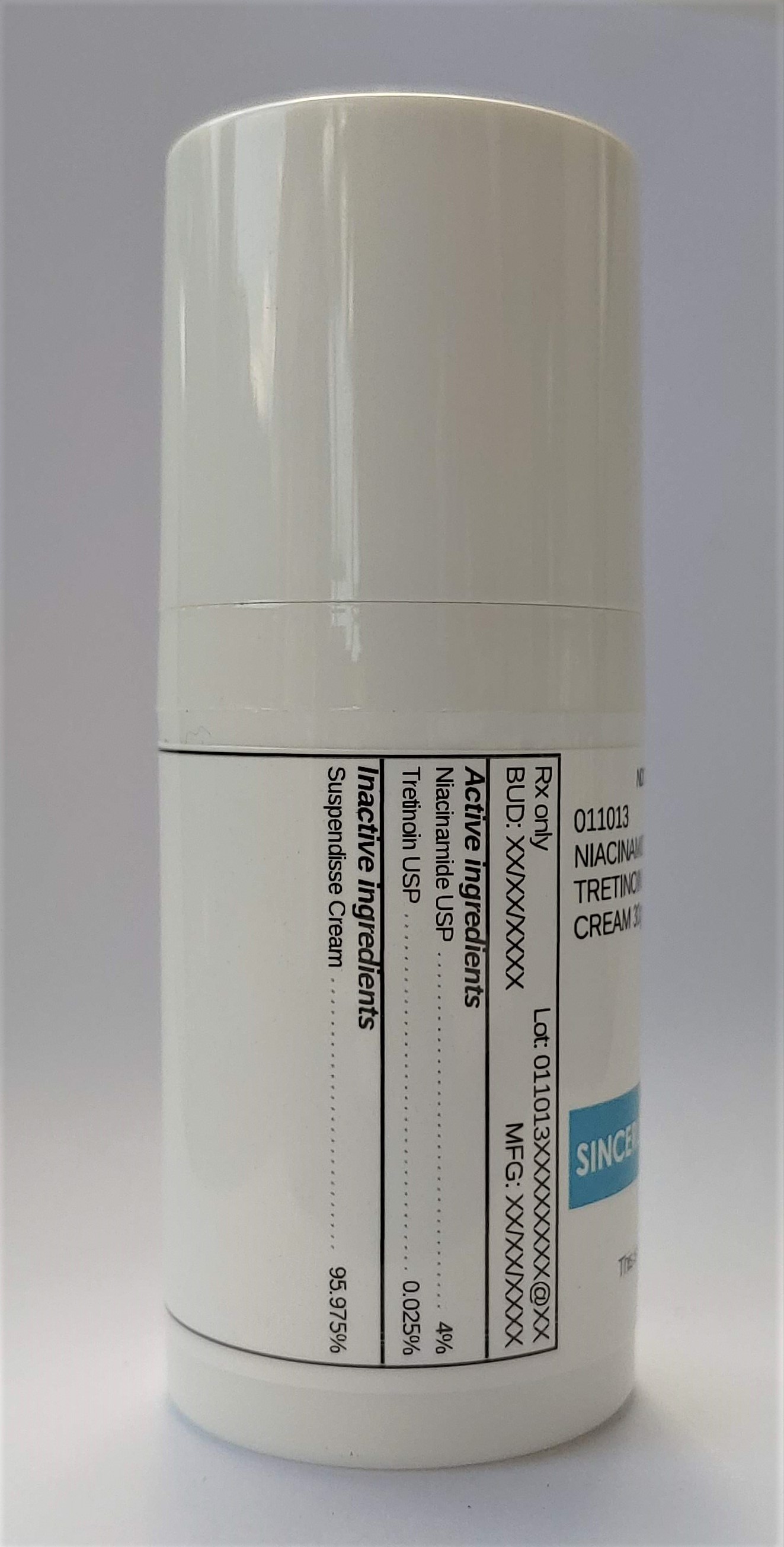 DRUG LABEL: 011013 NIACINAMIDE 4% / TRETINOIN 0.025%
NDC: 72934-2200 | Form: CREAM
Manufacturer: Sincerus Florida, LLC
Category: prescription | Type: HUMAN PRESCRIPTION DRUG LABEL
Date: 20200702

ACTIVE INGREDIENTS: NIACINAMIDE 4 g/100 g; TRETINOIN 0.025 g/100 g

011013 NIACINAMIDE 4% / TRETINOIN 0.025%